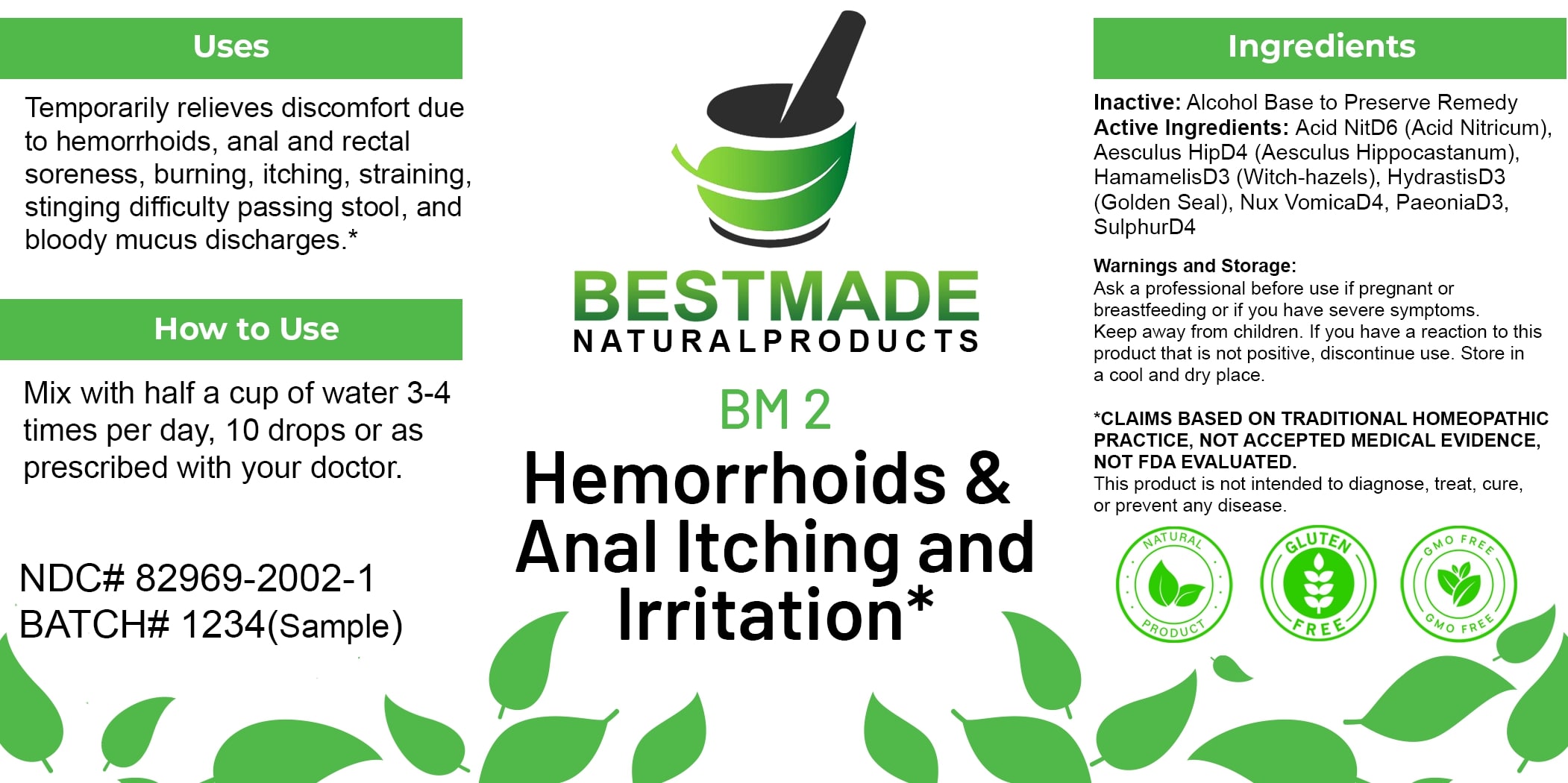 DRUG LABEL: Bestmade Natural Products BM2
NDC: 82969-2002 | Form: LIQUID
Manufacturer: Bestmade Natural Products
Category: homeopathic | Type: HUMAN OTC DRUG LABEL
Date: 20250122

ACTIVE INGREDIENTS: NITRIC ACID 30 [hp_C]/30 [hp_C]; HORSE CHESTNUT 30 [hp_C]/30 [hp_C]; STRYCHNOS NUX-VOMICA SEED 30 [hp_C]/30 [hp_C]; PAEONIA OFFICINALIS ROOT 30 [hp_C]/30 [hp_C]; SULFUR 30 [hp_C]/30 [hp_C]; GOLDENSEAL 30 [hp_C]/30 [hp_C]; HAMAMELIS VIRGINIANA ROOT BARK/STEM BARK 30 [hp_C]/30 [hp_C]
INACTIVE INGREDIENTS: ALCOHOL 30 [hp_C]/30 [hp_C]

BM2

DOSAGE AND ADMINISTRATION

How to Use

Mix with half a cup of water 3-4 times per day, 10 drops or as prescribed with your doctor.

INDICATIONS AND USAGE

Temporarily relieves discomfort due to hemorrhoids, anal and rectal soreness, burning, itching, straining, stinging difficulty passing stool, and bloody mucus discharges.*

*Claims Based on Traditional Homeopathic Practice, Not Accepted Medical Evidence, Not FDA Evaluated.
This product is not intended to diagnose, treat, cure, or prevent any disease.

Inactive:

Alcohol Base to Preserve Product

ACTIVE INGREDIENT

Acid NitD6 (Acid Nitricum), Aesculus HipD4 (Aesculus Hippocastanum), HamamelisD3 (Witch-hazels), HydrastisD3 (Golden Seal), Nux VomicaD4, PaeoniaD3, SulphurD4

KEEP OUT OF REACH OF CHILDREN

Warnings and Storage:
Ask a professional before use if pregnant or breastfeeding or if you have severe symptoms. Keep away from children. If you have a reaction to this product that is not positive, discontinue use. Store in a cool and dry place.

PURPOSE

Temporarily relieves discomfort due to hemorrhoids, anal and rectal soreness, burning, itching, straining, stinging difficulty passing stool, and bloody mucus discharges.*

*Claims Based on Traditional Homeopathic Practice, Not Accepted Medical Evidence, Not FDA Evaluated.
This product is not intended to diagnose, treat, cure, or prevent any disease.

Warnings and Storage:
Ask a professional before use if pregnant or breastfeeding or if you have severe symptoms. Keep away from children. If you have a reaction to this product that is not positive, discontinue use. Store in a cool and dry place.

Claims Based on Traditional Homeopathic Practice, Not Accepted Medical Evidence, Not FDA Evaluated.
This product is not intended to diagnose, treat, cure, or prevent any disease.

Entire package label